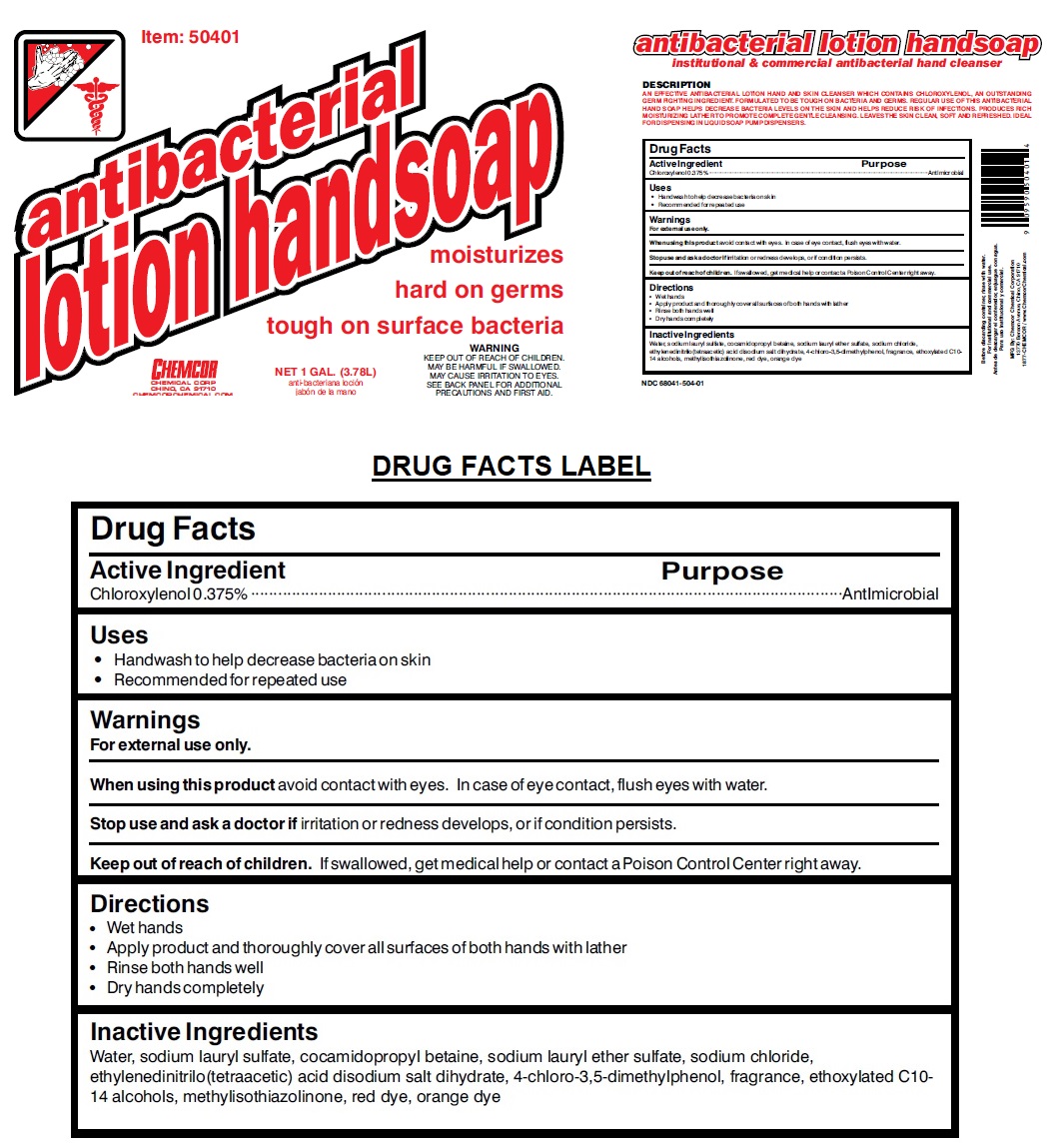 DRUG LABEL: Antibacterial Handsoap
NDC: 68041-504 | Form: LIQUID
Manufacturer: Chemcor Chemical Corporation
Category: otc | Type: HUMAN OTC DRUG LABEL
Date: 20230102

ACTIVE INGREDIENTS: CHLOROXYLENOL 0.00375 mg/1 mL
INACTIVE INGREDIENTS: WATER; SODIUM LAURYL SULFATE; COCAMIDOPROPYL BETAINE; SODIUM LAURETH-3 SULFATE; SODIUM CHLORIDE; EDETATE DISODIUM; C10-16 ALKETH-1; METHYLISOTHIAZOLINONE; FD&C RED NO. 40; ACID ORANGE 20

CHEMCOR antibacterial lotion handsoap

Active Ingredient

Chloroxylenol 0.375%

Purpose

Antimicrobial

Uses

• Handwash to help decrease bacteria on skin

• Recommended for repeated use

Warnings

For external use only.

When using this product avoid contact with eyes. In case of eye contact, flush eyes with water.

Stop use and ask a doctor if irritation or redness develops, or if condition persists.

Keep out of reach of children. If swallowed, get medical help or contact a Poison Control Center right away.

Directions

• Wet hands

• Apply product and thoroughly cover all surfaces of both hands with lather

• Rinse both hands well

• Dry hands completely

Inactive Ingredients

Water, sodium lauryl sulfate, cocamidopropyl betaine, sodium lauryl ether sulfate, sodium chloride, ethylenedinitrilo(tetraacetic) acid disodium salt dihydrate, 4-chloro-3,5-dimethylphenol, fragrance, ethoxylated C10-14 alcohols, methylisothiazolinone, red dye, orange dye

moisturizes

hard on germs

tough on surface bacteria

MAY BE HARMFUL IF SWALLOWED.

MAY CAUSE IRRITATION TO EYES.

SEE BACK PANEL FOR ADDITIONAL PRECAUTIONS AND FIRST AID.

institutional & commercial antibacterial hand cleanser

DESCRIPTION

AN EFFECTIVE ANTIBACTERIAL LOTION HAND AND SKIN CLEANSER WHICH CONTAINS CHLOROXYLENOL, AN OUTSTANDING GERM FIGHTING INGREDIENT. FORMULATED TO BE TOUGH ON BACTERIA AND GERMS. REGULAR USE OF THIS ANTIBACTERIAL HAND SOAP HELPS DECREASE BACTERIA LEVELS ON THE SKIN AND HELPS REDUCE RISK OF INFECTIONS. PRODUCES RICH MOISTURIZING LATHER TO PROMOTE COMPLETE GENTLE CLEANSING. LEAVES THE SKIN CLEAN, SOFT AND REFRESHED. IDEAL FOR DISPENSING IN LIQUID SOAP PUMP DISPENSERS.

Before discarding container, rinse with water.

For institutional and commercial use.

MFG By: Chemcor Chemical Corporation

13770 Benson Avenue, Chino, CA 91710

1877-CHEMCOR / www.ChemcorChemical.com